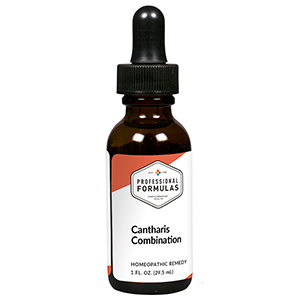 DRUG LABEL: Cantharis Combination
NDC: 63083-9252 | Form: LIQUID
Manufacturer: Professional Complementary Health Formulas
Category: homeopathic | Type: HUMAN OTC DRUG LABEL
Date: 20190815

ACTIVE INGREDIENTS: CHASTE TREE FRUIT 4 [hp_X]/29.5 mL; CINCHONA OFFICINALIS BARK 4 [hp_X]/29.5 mL; LYCOPODIUM CLAVATUM SPORE 4 [hp_X]/29.5 mL; PETROSELINUM CRISPUM ROOT 4 [hp_X]/29.5 mL; PICRIC ACID 6 [hp_X]/29.5 mL; LYTTA VESICATORIA 8 [hp_X]/29.5 mL; SELENIUM 10 [hp_X]/29.5 mL; SEPIA OFFICINALIS JUICE 10 [hp_X]/29.5 mL; CHLAMYDIA TRACHOMATIS 12 [hp_X]/29.5 mL
INACTIVE INGREDIENTS: ALCOHOL; WATER

R252

ACTIVE INGREDIENTS

Agnus castus 4X
Cinchona officinalis 4X
Lycopodium clavatum 4X
Petroselinum sativum 4X
Picricum acidum 6X
Cantharis 8X
Selenium metallicum 10X
Sepia 10X
Chlamydia 12X

QUESTIONS

Professional Formulas

PO Box 2034 Lake Oswego, OR 97035

INDICATIONS

For the temporary relief of urinary discomfort or difficulty, exhaustion or weakness, or itchy skin.*

PURPOSE

*Claims based on traditional homeopathic practice, not accepted medical evidence. Not FDA evaluated.

WARNINGS

Consult a doctor if condition worsens, if symptoms persist, or are accompanied by a fever, or bloody or cloudy urine. Keep out of the reach of children. In case of overdose, get medical help or contact a poison control center right away. If pregnant or breastfeeding, ask a healthcare professional before use.

Keep out of the reach of children.

PREGNANCY OR BREAST FEEDING

If pregnant or breastfeeding, ask a healthcare professional before use.

DIRECTIONS

Place drops under tongue 30 minutes before/after meals. Adults and children 12 years and over: Take 10 drops up to 3 times per day. Consult a physician for use in children under 12 years of age.

OTHER INFORMATION

Tamper resistant. If seal is broken, do not use. After opening, close container tightly and store at room temperature away from heat.

INACTIVE INGREDIENTS

40% ethanol, purified water.

LABEL

Est 1985

Professional Formulas

Complementary Health

Cantharis Combination

Homeopathic Remedy

1 FL. OZ. (29.5 mL)